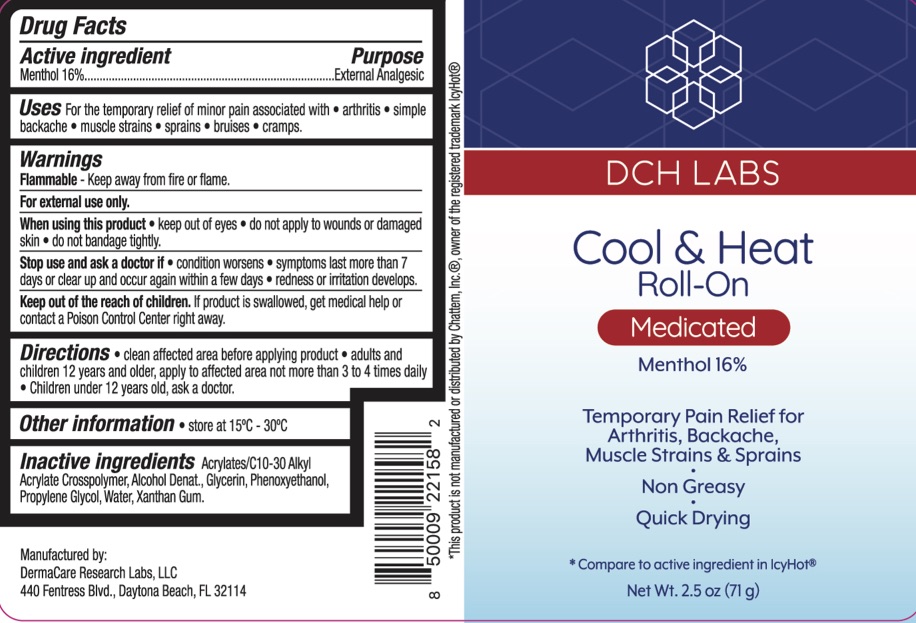 DRUG LABEL: DCH Labs Cool and Heat Roll-On
NDC: 72839-101 | Form: LIQUID
Manufacturer: Derma Care Research Labs, LLC
Category: otc | Type: HUMAN OTC DRUG LABEL
Date: 20241219

ACTIVE INGREDIENTS: MENTHOL 16 g/100 g
INACTIVE INGREDIENTS: PROPYLENE GLYCOL; ALCOHOL; PHENOXYETHANOL; WATER; GLYCERIN; CARBOMER INTERPOLYMER TYPE A (ALLYL SUCROSE CROSSLINKED); XANTHAN GUM

DCH Labs Cool & Heat Roll-On

ACTIVE INGREDIENT

Menthol 16%

PURPOSE

External Analgesic

INDICATIONS AND USAGE

For the temporary relief of minor pain associated with arthritis, simple backache, muscle strains, sprains, bruises, and cramps.

WARNINGS

For external use only. Flammable--Keep away from fire or flame. When using this product avoid contact with eyes, do not apply to wounds or damaged skin, and do not bandage tightly. Stop use and ask a doctor if condition worsens, if symptoms persist for more than 7 days or clear up and occur again within a few days.

KEEP OUT OF REACH OF CHILDREN

If swallowed, get medical help or contact a Poison Control Center right away.

DOSAGE AND ADMINISTRATION

Clean affected area before applying product. Adults and children 12 years of age and older, apply to the affected area not more than 3 to 4 times daily. Children under 12 years old ask a doctor.

INACTIVE INGREDIENT

Acrylates/C10-30 alkyl acrylate crosspolymer, alcohol denat., glycerin, phenoxyethanol, propylene glycol, water, xanthan gum.